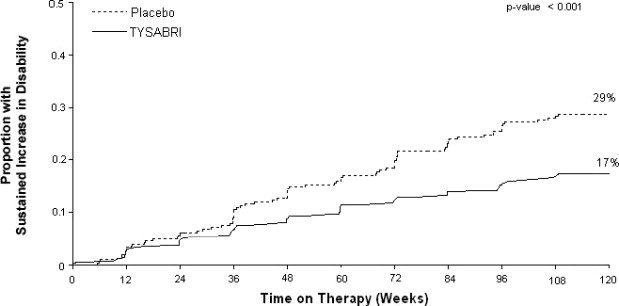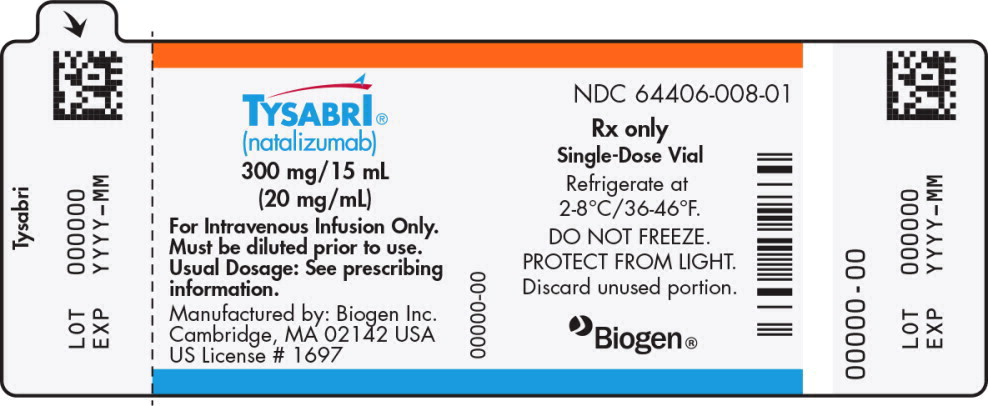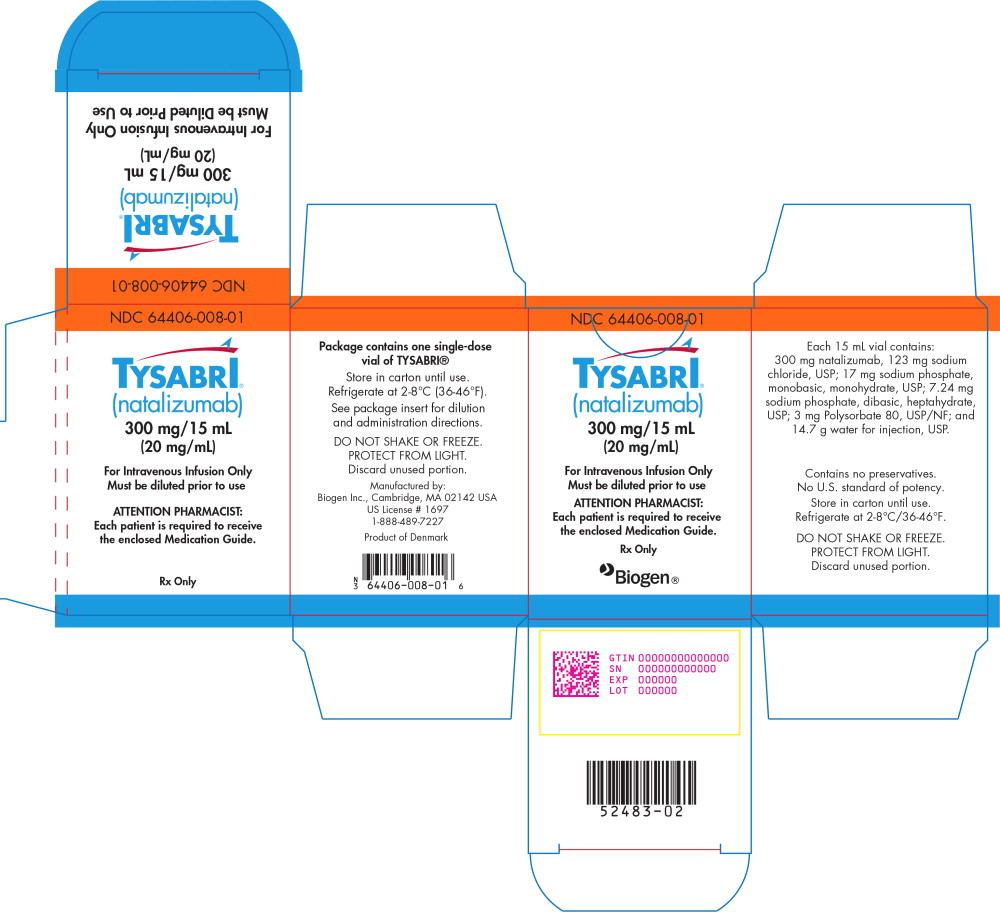 DRUG LABEL: TYSABRI
NDC: 64406-008 | Form: INJECTION
Manufacturer: Biogen Inc.
Category: prescription | Type: HUMAN PRESCRIPTION DRUG LABEL
Date: 20250321

ACTIVE INGREDIENTS: natalizumab 300 mg/15 mL
INACTIVE INGREDIENTS: sodium chloride; sodium phosphate, monobasic, monohydrate; sodium phosphate, dibasic, heptahydrate; polysorbate 80; water

HIGHLIGHTS OF PRESCRIBING INFORMATION

These highlights do not include all the information needed to use TYSABRI safely and effectively. See full prescribing information for TYSABRI.
TYSABRI (natalizumab) injection, for intravenous use
Initial U.S. Approval: 2004

RECENT MAJOR CHANGES

Warnings and Precautions (5.8) | 3/2025

WARNING: PROGRESSIVE MULTIFOCAL LEUKOENCEPHALOPATHY

See full prescribing information for complete boxed warning

- TYSABRI increases the risk of progressive multifocal leukoencephalopathy (PML), an opportunistic viral infection of the brain that usually leads to death or severe disability (5.1)
- Risk factors for the development of PML include the presence of anti-JCV antibodies, duration of therapy, and prior use of immunosuppressants. These factors should be considered in the context of expected benefit when initiating and continuing treatment with TYSABRI (5.1)
- Monitor patients, and withhold TYSABRI immediately at the first sign or symptom suggestive of PML (4, 5.1)
- Because of the risk of PML, TYSABRI is available only through a restricted distribution program called the TOUCH® Prescribing Program (5.1, 5.2)

1 INDICATIONS AND USAGE

TYSABRI is an integrin receptor antagonist indicated for treatment of:

Multiple Sclerosis (MS)

TYSABRI is indicated as monotherapy for the treatment of relapsing forms of multiple sclerosis, to include clinically isolated syndrome, relapsing-remitting disease, and active secondary progressive disease, in adults. TYSABRI increases the risk of PML [See Warnings and Precautions (5.1)]. When initiating and continuing treatment with TYSABRI, physicians should consider whether the expected benefit of TYSABRI is sufficient to offset this risk. (1.1)

Crohn's Disease (CD)

- TYSABRI is indicated for inducing and maintaining clinical response and remission in adult patients with moderately to severely active Crohn's disease with evidence of inflammation who have had an inadequate response to, or are unable to tolerate, conventional CD therapies and inhibitors of TNF-α. (1.2)

Important Limitations:

- In CD, TYSABRI should not be used in combination with immunosuppressants or inhibitors of TNF-α. (1.2)

2 DOSAGE AND ADMINISTRATION

- 300 mg infused intravenously over one hour, every four weeks. Do not give as an intravenous push or bolus (2.1, 2.2)
- TYSABRI solution must be administered within 48 hours of preparation (2.3)
- Observe patients during all infusions. Post-infusion, for the first 12 infusions, observe patients for one hour after the infusion is complete. For patients who have received 12 infusions without evidence of a hypersensitivity reaction, observe patients post-infusion for the 13th and subsequent infusions according to clinical judgment. (2.4)
- In CD, discontinue in patients that have not experienced therapeutic benefit by 12 weeks of induction therapy, and in patients that cannot discontinue chronic concomitant steroids within six months of starting therapy (2.2)

3 DOSAGE FORMS AND STRENGTHS

Injection: 300 mg/15 mL (20 mg/mL) solution in a single-dose vial for dilution prior to infusion (3)

4 CONTRAINDICATIONS

- Patients who have or have had PML (4)
- Patients who have had a hypersensitivity reaction to TYSABRI (4, 5.3)

5 WARNINGS AND PRECAUTIONS

- Herpes infections: Life-threatening and fatal cases have occurred with herpes encephalitis and meningitis infections. Blindness has occurred in patients developing acute retinal necrosis. Discontinue TYSABRI if these infections occur and treat appropriately (5.3)
- Hepatotoxicity: Significant liver injury, including liver failure requiring transplant, has occurred. Discontinue TYSABRI in patients with evidence of liver injury (5.4)
- Hypersensitivity reactions: Serious hypersensitivity reactions (e.g., anaphylaxis) have occurred. Permanently discontinue TYSABRI if such a reaction occurs (5.5)
- Immunosuppression/Infections: TYSABRI may increase the risk for certain infections. Monitor patients for development of infections due to increased risk with use of TYSABRI (5.6)
- Hematological Abnormalities: TYSABRI may cause thrombocytopenia. Monitor patients for bleeding abnormalities. Discontinue TYSABRI in patients with thrombocytopenia. Neonatal thrombocytopenia and anemia have also occurred. Obtain a complete blood count in neonates exposed to TYSABRI in utero. (5.8)

6 ADVERSE REACTIONS

Most common adverse reactions (incidence ≥ 10%):

- MS - headache, fatigue, arthralgia, urinary tract infection, lower respiratory tract infection, gastroenteritis, vaginitis, depression, pain in extremity, abdominal discomfort, diarrhea NOS, and rash (6.1)
- CD - headache, upper respiratory tract infections, nausea, and fatigue (6.1)

To report SUSPECTED ADVERSE REACTIONS, contact Biogen at 1-800-456-2255 or FDA at 1-800-FDA-1088 or www.fda.gov/medwatch.

8 USE IN SPECIFIC POPULATIONS

Pregnancy: Can cause fetal harm. (5.8, 8.1)

FULL PRESCRIBING INFORMATION

WARNING: PROGRESSIVE MULTIFOCAL LEUKOENCEPHALOPATHY

TYSABRI increases the risk of progressive multifocal leukoencephalopathy (PML), an opportunistic viral infection of the brain that usually leads to death or severe disability. Risk factors for the development of PML include the presence of anti-JCV antibodies, duration of therapy, and prior use of immunosuppressants. These factors should be considered in the context of expected benefit when initiating and continuing treatment with TYSABRI [see Warnings and Precautions (5.1)].

- Healthcare professionals should monitor patients on TYSABRI for any new sign or symptom that may be suggestive of PML. TYSABRI dosing should be withheld immediately at the first sign or symptom suggestive of PML. For diagnosis, an evaluation that includes a gadolinium-enhanced magnetic resonance imaging (MRI) scan of the brain and, when indicated, cerebrospinal fluid analysis for JC viral DNA are recommended [see Contraindications (4), Warnings and Precautions (5.1)].
- Because of the risk of PML, TYSABRI is available only through a restricted program under a Risk Evaluation and Mitigation Strategy (REMS) called the TOUCH® Prescribing Program [see Warnings and Precautions (5.2)].

1 INDICATIONS AND USAGE

1.1 Multiple Sclerosis (MS)

TYSABRI is indicated as monotherapy for the treatment of relapsing forms of multiple sclerosis, to include clinically isolated syndrome, relapsing-remitting disease, and active secondary progressive disease, in adults. TYSABRI increases the risk of PML [see Warnings and Precautions (5.1)]. When initiating and continuing treatment with TYSABRI, physicians should consider whether the expected benefit of TYSABRI is sufficient to offset this risk.

1.2 Crohn's Disease (CD)

TYSABRI is indicated for inducing and maintaining clinical response and remission in adult patients with moderately to severely active Crohn's disease with evidence of inflammation who have had an inadequate response to, or are unable to tolerate, conventional CD therapies and inhibitors of TNF-α. TYSABRI should not be used in combination with immunosuppressants (e.g., 6-mercaptopurine, azathioprine, cyclosporine, or methotrexate) or inhibitors of TNF-α [see Warnings and Precautions (5.1)].

2 DOSAGE AND ADMINISTRATION

2.1 Multiple Sclerosis (MS)

Only prescribers registered in the MS TOUCH® Prescribing Program may prescribe TYSABRI for multiple sclerosis [see Warnings and Precautions (5.2)]. The recommended dose of TYSABRI for multiple sclerosis is 300 mg intravenous infusion over one hour every four weeks.

2.2 Crohn's Disease (CD)

Only prescribers registered in the CD TOUCH® Prescribing Program may prescribe TYSABRI for Crohn's disease [see Warnings and Precautions (5.2)].

The recommended dose of TYSABRI for Crohn's disease is 300 mg intravenous infusion over one hour every four weeks. TYSABRI should not be used with concomitant immunosuppressants (e.g., 6-mercaptopurine, azathioprine, cyclosporine, or methotrexate) or concomitant inhibitors of TNF-α. Aminosalicylates may be continued during treatment with TYSABRI.

If the patient with Crohn's disease has not experienced therapeutic benefit by 12 weeks of induction therapy, discontinue TYSABRI. For patients with Crohn's disease who start TYSABRI while on chronic oral corticosteroids, commence steroid tapering as soon as a therapeutic benefit of TYSABRI has occurred; if the patient with Crohn's disease cannot be tapered off of oral corticosteroids within six months of starting TYSABRI, discontinue TYSABRI. Other than the initial six-month taper, prescribers should consider discontinuing TYSABRI for patients who require additional steroid use that exceeds three months in a calendar year to control their Crohn's disease.

2.3 Dilution Instructions

1. Use aseptic technique when preparing TYSABRI solution for intravenous infusion. Each vial is intended for single use only. Discard any unused portion.
2. TYSABRI is a colorless, clear to slightly opalescent solution. Inspect the TYSABRI vial for particulate material and discoloration prior to dilution and administration. If visible particulates are observed and/or the liquid in the vial is discolored, the vial must not be used.
3. To prepare the diluted solution, withdraw 15 mL of TYSABRI from the vial using a sterile needle and syringe. Inject TYSABRI into 100 mL of 0.9% Sodium Chloride Injection, USP. No other intravenous diluents may be used to prepare the TYSABRI diluted solution.
4. Gently invert the TYSABRI diluted solution to mix completely. Do not shake. Inspect the solution visually for particulate material prior to administration.
5. The final dosage diluted solution has a concentration of 2.6 mg/mL.
6. Following dilution, infuse TYSABRI solution immediately, or refrigerate the diluted solution at 2°C to 8°C, and use within 48 hours. If stored at 2°C to 8°C, allow the diluted solution to warm to room temperature prior to infusion. DO NOT FREEZE.

2.4 Administration Instructions

- Infuse TYSABRI 300 mg in 100 mL 0.9% Sodium Chloride Injection, USP, over approximately one hour (infusion rate approximately 5 mg per minute). Do not administer TYSABRI as an intravenous push or bolus injection. After the infusion is complete, flush with 0.9% Sodium Chloride Injection, USP.
- Observe patients during all infusions. Promptly discontinue the infusion upon the first observation of any signs or symptoms consistent with a hypersensitivity-type reaction [see Warnings and Precautions (5.5)].
- Post-infusion, for the first 12 infusions, observe patients for one hour after the infusion is complete. For patients who have received 12 infusions without evidence of a hypersensitivity reaction, observe patients post-infusion for the 13th and subsequent infusions according to clinical judgment.
- Use of filtration devices during administration has not been evaluated. Other medications should not be injected into infusion set side ports or mixed with TYSABRI.

3 DOSAGE FORMS AND STRENGTHS

Injection: 300 mg /15 mL (20 mg/mL) colorless and clear to slightly opalescent solution in a single-dose vial for dilution prior to infusion.

4 CONTRAINDICATIONS

- TYSABRI is contraindicated in patients who have or have had progressive multifocal leukoencephalopathy (PML) [see Warnings and Precautions (5.1)].
- TYSABRI is contraindicated in patients who have had a hypersensitivity reaction to TYSABRI. Observed reactions range from urticaria to anaphylaxis [see Warnings and Precautions (5.5)].

5 WARNINGS AND PRECAUTIONS

5.1 Progressive Multifocal Leukoencephalopathy

Progressive multifocal leukoencephalopathy (PML), an opportunistic viral infection of the brain caused by the JC virus (JCV) that typically only occurs in patients who are immunocompromised, and that usually leads to death or severe disability, has occurred in patients who have received TYSABRI.

Three factors that are known to increase the risk of PML in TYSABRI-treated patients have been identified:

- The presence of anti-JCV antibodies. Patients who are anti-JCV antibody positive have a higher risk for developing PML.
- Longer treatment duration, especially beyond 2 years.
- Prior treatment with an immunosuppressant (e.g., mitoxantrone, azathioprine, methotrexate, cyclophosphamide, mycophenolate mofetil).

These factors should be considered in the context of expected benefit when initiating and continuing treatment with TYSABRI.

Table 1: Estimated United States Incidence of PML Stratified by Risk Factor
Anti-JCV Antibody Negative | TYSABRI Exposure | Anti-JCV Antibody Positive
Anti-JCV Antibody Negative | TYSABRI Exposure | No Prior Immunosuppressant Use | Prior Immunosuppressant Use
1/10,000 | 1-24 months | <1/1,000 | 1/1,000
1/10,000 | 25-48 months | 2/1,000 | 6/1,000
1/10,000 | 49-72 months | 4/1,000 | 7/1,000
1/10,000 | 73-96 months | 2/1,000 | 6/1,000
Notes: The risk estimates are based on postmarketing data in the United States from approximately 100,000 TYSABRI exposed patients.
The anti-JCV antibody status was determined using an anti-JCV antibody test (ELISA) that has been analytically and clinically validated and is configured with detection and inhibition steps to confirm the presence of JCV-specific antibodies with an analytical false negative rate of 3%.

Retrospective analyses of postmarketing data from various sources, including observational studies and spontaneous reports obtained worldwide, suggest that the risk of developing PML may be associated with relative levels of serum anti-JCV antibody compared to a calibrator as measured by ELISA (often described as an anti-JCV antibody index value).

Ordinarily, patients receiving chronic immunosuppressant or immunomodulatory therapy or who have systemic medical conditions resulting in significantly compromised immune system function should not be treated with TYSABRI. Infection by the JC virus is required for the development of PML. Anti-JCV antibody testing should not be used to diagnose PML. Anti-JCV antibody negative status indicates that antibodies to the JC virus have not been detected. Patients who are anti-JCV antibody negative have a lower risk of PML than those who are positive. Patients who are anti-JCV antibody negative are still at risk for the development of PML due to the potential for a new JCV infection or a false negative test result. The reported rate of seroconversion in patients with MS (changing from anti-JCV antibody negative to positive and remaining positive in subsequent testing) is 3 to 8 percent annually. In addition, some patients' serostatus may change intermittently. Therefore, patients with a negative anti-JCV antibody test result should be retested periodically. For purposes of risk assessment, a patient with a positive anti-JCV antibody test at any time is considered anti-JCV antibody positive regardless of the results of any prior or subsequent anti-JCV antibody testing. When assessed, anti-JCV antibody status should be determined using an analytically and clinically validated immunoassay. After plasma exchange (PLEX), wait at least two weeks to test for anti-JCV antibodies to avoid false negative test results caused by the removal of serum antibodies. After infusion of intravenous immunoglobulin (IVIg), wait at least 6 months (5 half-lives) for the IVIg to clear in order to avoid false positive anti-JCV antibody test results.

Healthcare professionals should monitor patients on TYSABRI for any new sign or symptom suggestive of PML. Symptoms associated with PML are diverse, progress over days to weeks, and include progressive weakness on one side of the body or clumsiness of limbs, disturbance of vision, and changes in thinking, memory, and orientation leading to confusion and personality changes. The progression of deficits usually leads to death or severe disability over weeks or months. Withhold TYSABRI dosing immediately and perform an appropriate diagnostic evaluation at the first sign or symptom suggestive of PML.

MRI findings may be apparent before clinical signs or symptoms. Cases of PML, diagnosed based on MRI findings and the detection of JCV DNA in the cerebrospinal fluid in the absence of clinical signs or symptoms specific to PML, have been reported. Many of these patients subsequently became symptomatic with PML. Therefore, monitoring with MRI for signs that may be consistent with PML may be useful, and any suspicious findings should lead to further investigation to allow for an early diagnosis of PML, if present. Consider monitoring patients at high risk for PML more frequently. Lower PML-related mortality and morbidity have been reported following TYSABRI discontinuation in patients with PML who were initially asymptomatic compared to patients with PML who had characteristic clinical signs and symptoms at diagnosis. It is not known whether these differences are due to early detection and discontinuation of TYSABRI or due to differences in disease in these patients.

There are no known interventions that can reliably prevent PML or that can adequately treat PML if it occurs. PML has been reported following discontinuation of TYSABRI in patients who did not have findings suggestive of PML at the time of discontinuation. Patients should continue to be monitored for any new signs or symptoms that may be suggestive of PML for at least six months following discontinuation of TYSABRI.

Because of the risk of PML, TYSABRI is available only under a restricted distribution program, the TOUCH® Prescribing Program.

In multiple sclerosis patients, an MRI scan should be obtained prior to initiating therapy with TYSABRI. This MRI may be helpful in differentiating subsequent multiple sclerosis symptoms from PML.

In Crohn's disease patients, a baseline brain MRI may also be helpful to distinguish pre-existent lesions from newly developed lesions, but brain lesions at baseline that could cause diagnostic difficulty while on TYSABRI therapy are uncommon.

For diagnosis of PML, an evaluation including a gadolinium-enhanced MRI scan of the brain and, when indicated, cerebrospinal fluid analysis for JC viral DNA are recommended. If the initial evaluations for PML are negative but clinical suspicion for PML remains, continue to withhold TYSABRI dosing, and repeat the evaluations.

There are no known interventions that can adequately treat PML if it occurs. Three sessions of PLEX over 5 to 8 days were shown to accelerate TYSABRI clearance in a study of 12 patients with MS who did not have PML, although in the majority of patients, alpha-4 integrin receptor binding remained high. Adverse events which may occur during PLEX include clearance of other medications and volume shifts, which have the potential to lead to hypotension or pulmonary edema. Although PLEX has not been prospectively studied in TYSABRI-treated patients with PML, it has been used in such patients in the postmarketing setting to remove TYSABRI more quickly from the circulation. There is no evidence that PLEX has any benefit in the treatment of opportunistic infections such as PML.

JC virus infection of granule cell neurons in the cerebellum (i.e., JC virus granule cell neuronopathy [JCV GCN]) has been reported in patients treated with TYSABRI. JCV GCN can occur with or without concomitant PML. JCV GCN can cause cerebellar dysfunction (e.g., ataxia, incoordination, apraxia, visual disorders), and neuroimaging can show cerebellar atrophy. For diagnosis of JCV GCN, an evaluation that includes a gadolinium-enhanced MRI scan of the brain and, when indicated, cerebrospinal fluid analysis for JC viral DNA, is recommended. JCV GCN should be managed similarly to PML.

Immune reconstitution inflammatory syndrome (IRIS) has been reported in the majority of TYSABRI treated patients who developed PML and subsequently discontinued TYSABRI. In almost all cases, IRIS occurred after PLEX was used to eliminate circulating TYSABRI. It presents as a clinical decline in the patient's condition after TYSABRI removal (and in some cases after apparent clinical improvement) that may be rapid, can lead to serious neurological complications or death, and is often associated with characteristic changes in the MRI. TYSABRI has not been associated with IRIS in patients discontinuing treatment with TYSABRI for reasons unrelated to PML. In TYSABRI treated patients with PML, IRIS has been reported within days to several weeks after PLEX. Monitoring for development of IRIS and appropriate treatment of the associated inflammation should be undertaken.

5.2 TYSABRI TOUCH® Prescribing Program

TYSABRI is available only through a restricted program under a REMS called the TOUCH® Prescribing Program because of the risk of PML [see Warnings and Precautions (5.1)].

For prescribers and patients, the TOUCH® Prescribing Program has two components: MS TOUCH® (for patients with multiple sclerosis) and CD TOUCH® (for patients with Crohn's disease).

Selected requirements of the TOUCH® Prescribing Program include the following:

- Prescribers must be certified and comply with the following:
  - Review the TOUCH® Prescribing Program prescriber educational materials, including the full prescribing information.
  - Review, complete, and sign the Prescriber Enrollment Form.
  - Educate patients on the benefits and risks of treatment with TYSABRI, ensure that patients receive the Medication Guide, and encourage them to ask questions.
  - Review, complete, and sign the Patient Enrollment Form for each patient.
  - Evaluate patients three months after the first infusion, six months after the first infusion, every six months thereafter, and for at least six months after discontinuing TYSABRI.
  - Determine every six months whether patients should continue on treatment and, if so, authorize treatment for another six months.
  - Submit to Biogen the “TYSABRI Patient Status Report and Reauthorization Questionnaire” six months after initiating treatment and every six months thereafter.
  - Complete an “Initial Discontinuation Questionnaire” when TYSABRI is discontinued, and a “6-Month Discontinuation Questionnaire” following discontinuation of TYSABRI.
  - Report cases of PML, hospitalizations due to opportunistic infections, and deaths to Biogen at 1-800-456-2255 as soon as possible.
- Patients must be enrolled in the TOUCH® Prescribing Program, read the Medication Guide, understand the risks associated with TYSABRI, and complete and sign the Patient Enrollment Form.
- Pharmacies and infusion centers must be specially certified to dispense or infuse TYSABRI.

5.3 Herpes Infections

Herpes Encephalitis and Meningitis

TYSABRI increases the risk of developing encephalitis and meningitis caused by herpes simplex and varicella zoster viruses. Serious, life-threatening, and sometimes fatal cases have been reported in the postmarketing setting in multiple sclerosis patients receiving TYSABRI. Laboratory confirmation in those cases was based on positive PCR for viral DNA in the cerebrospinal fluid. The duration of treatment with TYSABRI prior to onset ranged from a few months to several years. Monitor patients receiving TYSABRI for signs and symptoms of meningitis and encephalitis. If herpes encephalitis or meningitis occurs, TYSABRI should be discontinued, and appropriate treatment for herpes encephalitis/meningitis should be administered.

Acute Retinal Necrosis

Acute retinal necrosis (ARN) is a fulminant viral infection of the retina caused by the family of herpes viruses (e.g., varicella zoster, herpes simplex virus). A higher risk of ARN has been observed in patients being administered TYSABRI. Patients presenting with eye symptoms, including decreased visual acuity, redness, or eye pain, should be referred for retinal screening for ARN. Some ARN cases occurred in patients with central nervous system (CNS) herpes infections (e.g., herpes meningitis or encephalitis). Serious cases of ARN led to blindness of one or both eyes in some patients. Following clinical diagnosis of ARN, consider discontinuation of TYSABRI. The treatment reported in ARN cases included anti-viral therapy and, in some cases, surgery.

5.4 Hepatotoxicity

Clinically significant liver injury, including acute liver failure requiring transplant, has been reported in patients treated with TYSABRI in the postmarketing setting. Signs of liver injury, including markedly elevated serum hepatic enzymes and elevated total bilirubin, occurred as early as six days after the first dose; signs of liver injury have also been reported for the first time after multiple doses. In some patients, liver injury recurred upon rechallenge, providing evidence that TYSABRI caused the injury. The combination of transaminase elevations and elevated bilirubin without evidence of obstruction is generally recognized as an important predictor of severe liver injury that may lead to death or the need for a liver transplant in some patients.

TYSABRI should be discontinued in patients with jaundice or other evidence of significant liver injury (e.g., laboratory evidence).

5.5 Hypersensitivity/Antibody Formation

Hypersensitivity reactions have occurred in patients receiving TYSABRI, including serious systemic reactions (e.g., anaphylaxis), which occurred at an incidence of <1%. These reactions usually occur within two hours of the start of the infusion. Symptoms associated with these reactions can include urticaria, dizziness, fever, rash, rigors, pruritus, nausea, flushing, hypotension, dyspnea, and chest pain. Generally, these reactions are associated with antibodies to TYSABRI.

If a hypersensitivity reaction occurs, discontinue administration of TYSABRI, and initiate appropriate therapy. Patients who experience a hypersensitivity reaction should not be re-treated with TYSABRI. Hypersensitivity reactions were more frequent in patients with antibodies to TYSABRI compared to patients who did not develop antibodies to TYSABRI in both MS and CD studies. Therefore, the possibility of antibodies to TYSABRI should be considered in patients who have hypersensitivity reactions [see Adverse Reactions (6.2)].

Antibody testing: If the presence of persistent antibodies is suspected, antibody testing should be performed. Antibodies may be detected and confirmed with sequential serum antibody tests. Antibodies detected early in the treatment course (e.g., within the first six months) may be transient and may disappear with continued dosing. It is recommended that testing be repeated three months after an initial positive result to confirm that antibodies are persistent. Prescribers should consider the overall benefits and risks of TYSABRI in a patient with persistent antibodies.

Patients who receive TYSABRI for a short exposure (1 to 2 infusions) followed by an extended period without treatment are at higher risk of developing anti-natalizumab antibodies and/or hypersensitivity reactions on re-exposure, compared to patients who received regularly scheduled treatment. Given that patients with persistent antibodies to TYSABRI experience reduced efficacy, and that hypersensitivity reactions are more common in such patients, consideration should be given to testing for the presence of antibodies in patients who wish to recommence therapy following a dose interruption. Following a period of dose interruption, patients testing negative for antibodies prior to re-dosing have a risk of antibody development with re-treatment that is similar to TYSABRI naïve patients [see Adverse Reactions (6.2)].

5.6 Immunosuppression/Infections

The immune system effects of TYSABRI may increase the risk for infections. In Study MS1 [see Clinical Studies (14.1)], certain types of infections, including pneumonias and urinary tract infections (including serious cases), gastroenteritis, vaginal infections, tooth infections, tonsillitis, and herpes infections, occurred more often in TYSABRI-treated patients than in placebo-treated patients [see Warnings and Precautions (5.1), Adverse Reactions (6.1)]. One opportunistic infection, a cryptosporidial gastroenteritis with a prolonged course, was observed in a patient who received TYSABRI in Study MS1.

In Studies MS1 and MS2, an increase in infections was seen in patients concurrently receiving short courses of corticosteroids. However, the increase in infections in TYSABRI-treated patients who received steroids was similar to the increase in placebo-treated patients who received steroids.

In a long-term safety study of patients treated with TYSABRI for multiple sclerosis, opportunistic infections (pulmonary mycobacterium avium intracellulare, aspergilloma, cryptococcal fungemia and meningitis, and Candida pneumonia) have been observed in <1% of TYSABRI-treated patients.

In CD clinical studies, opportunistic infections (pneumocystis carinii pneumonia, pulmonary mycobacterium avium intracellulare, bronchopulmonary aspergillosis, and burkholderia cepacia) have been observed in <1% of TYSABRI-treated patients; some of these patients were receiving concurrent immunosuppressants [see Warnings and Precautions (5.1), Adverse Reactions (6.1)].

In Studies CD1 and CD2, an increase in infections was seen in patients concurrently receiving corticosteroids. However, the increase in infections was similar in placebo-treated and TYSABRI-treated patients who received steroids. Concurrent use of antineoplastic, immunosuppressant, or immunomodulating agents may further increase the risk of infections, including PML and other opportunistic infections, over the risk observed with use of TYSABRI alone [see Warnings and Precautions (5.1), Adverse Reactions (6.1)]. The safety and efficacy of TYSABRI in combination with antineoplastic, immunosuppressant, or immunomodulating agents have not been established. Patients receiving chronic immunosuppressant or immunomodulatory therapy or who have systemic medical conditions resulting in significantly compromised immune system function should not ordinarily be treated with TYSABRI. The risk of PML is also increased in patients who have been treated with an immunosuppressant prior to receiving TYSABRI [see Warnings and Precautions (5.1)].

For patients with Crohn's disease who start TYSABRI while on chronic corticosteroids, commence steroid withdrawal as soon as a therapeutic benefit has occurred. If the patient cannot discontinue systemic corticosteroids within six months, discontinue TYSABRI.

5.7 Laboratory Test Abnormalities

In clinical trials, TYSABRI was observed to induce increases in circulating lymphocytes, monocytes, eosinophils, basophils, and nucleated red blood cells. Observed changes persisted during TYSABRI exposure, but were reversible, returning to baseline levels usually within 16 weeks after the last dose. Elevations of neutrophils were not observed. TYSABRI induces mild decreases in hemoglobin levels (mean decrease of 0.6 g/dL) that are frequently transient.

5.8 Hematological Abnormalities

Cases of thrombocytopenia, including immune thrombocytopenic purpura (ITP), have been reported with the use of TYSABRI in the postmarketing setting. Symptoms of thrombocytopenia may include easy bruising, abnormal bleeding, and petechiae. Delay in the diagnosis and treatment of thrombocytopenia may lead to serious and life-threatening sequelae. If thrombocytopenia is suspected, TYSABRI should be discontinued.

Cases of neonatal thrombocytopenia and anemia have been reported in newborns with in utero exposure to TYSABRI [see Use in Specific Populations (8.1)]. A CBC should be obtained in neonates with in utero exposure to TYSABRI.

5.9 Immunizations

No data are available on the effects of vaccination in patients receiving TYSABRI. No data are available on the secondary transmission of infection by live vaccines in patients receiving TYSABRI.

6 ADVERSE REACTIONS

The following serious adverse reactions are described below and elsewhere in the labeling:

- Progressive Multifocal Leukoencephalopathy (PML) [see Warnings and Precautions (5.1)]
- Herpes Infections [see Warnings and Precautions (5.3)]
- Hepatotoxicity [see Warnings and Precautions (5.4)]
- Hypersensitivity/Antibody Formation [see Warnings and Precautions (5.5)]
- Immunosuppression/Infections [see Warnings and Precautions (5.6)]
- Hematological Abnormalities [see Warnings and Precautions (5.8)]

6.1 Clinical Trials Experience

Because clinical trials are conducted under widely varying conditions, adverse reaction rates observed in the clinical trials of a drug cannot be directly compared to rates in the clinical trials of another drug and may not reflect the rates observed in practice.

The most common adverse reactions (incidence ≥ 10%) were headache and fatigue in both the multiple sclerosis (MS) and Crohn's disease (CD) studies. Other common adverse reactions (incidence ≥ 10%) in the MS population were arthralgia, urinary tract infection, lower respiratory tract infection, gastroenteritis, vaginitis, depression, pain in extremity, abdominal discomfort, diarrhea NOS, and rash. Other common adverse reactions (incidence ≥ 10%) in the CD population were upper respiratory tract infections and nausea.

The most frequently reported adverse reactions resulting in clinical intervention (i.e., discontinuation of TYSABRI) in the MS studies were urticaria (1%) and other hypersensitivity reactions (1%), and in the CD studies (Studies CD1 and CD2) were the exacerbation of Crohn's disease (4.2%) and acute hypersensitivity reactions (1.5%) [see Warnings and Precautions (5.5)].

A total of 1617 multiple sclerosis patients in controlled studies received TYSABRI, with a median duration of exposure of 28 months. A total of 1563 patients received TYSABRI in all CD studies for a median exposure of 5 months; of these patients, 33% (n=518) received at least one year of treatment and 19% (n=297) received at least two years of treatment.

Multiple Sclerosis Clinical Studies

The most common serious adverse reactions in Study MS1 [see Clinical Studies (14.1)] with TYSABRI were infections (3.2% versus 2.6% in placebo, including urinary tract infection [0.8% versus 0.3%] and pneumonia [0.6% versus 0%]), acute hypersensitivity reactions (1.1% versus 0.3%, including anaphylaxis/anaphylactoid reaction [0.8% versus 0%]), depression (1.0% versus 1.0%, including suicidal ideation or attempt [0.6% versus 0.3%]), and cholelithiasis (1.0% versus 0.3%). In Study MS2, serious adverse reactions of appendicitis were also more common in patients who received TYSABRI (0.8% versus 0.2% in placebo).

Table 2 enumerates adverse reactions and selected laboratory abnormalities that occurred in Study MS1 at an incidence of at least 1 percentage point higher in TYSABRI-treated patients than was observed in placebo-treated patients.

Table 2: Adverse Reactions in Study MS1 (Monotherapy Study)
Adverse Reactions (Preferred Term) | TYSABRI n=627 % | Placebo n=312 %
General
Headache | 38 | 33
Fatigue | 27 | 21
Arthralgia | 19 | 14
Chest discomfort | 5 | 3
Other hypersensitivity reactions** | 5 | 2
Acute hypersensitivity reactions** | 4 | <1
Seasonal allergy | 3 | 2
Rigors | 3 | <1
Weight increased | 2 | <1
Weight decreased | 2 | <1
Infection
Urinary tract infection | 21 | 17
Lower respiratory tract infection | 17 | 16
Gastroenteritis | 11 | 9
Vaginitis* | 10 | 6
Tooth infections | 9 | 7
Herpes | 8 | 7
Tonsillitis | 7 | 5
Psychiatric
Depression | 19 | 16
Musculoskeletal/Connective Tissue Disorders
Pain in extremity Muscle cramp Joint swelling | 16 5 2 | 14 3 1
Gastrointestinal Abdominal discomfort Diarrhea NOS Abnormal liver function test | 11 10 5 | 10 9 4
Skin Rash Dermatitis Pruritus Night sweats | 12 7 4 1 | 9 4 2 0
Menstrual Disorders* Irregular menstruation Dysmenorrhea Amenorrhea Ovarian cyst | 5 3 2 2 | 4 <1 1 <1
Neurologic Disorders Vertigo Somnolence | 6 2 | 5 <1
Renal and Urinary Disorders Urinary urgency/frequency Urinary incontinence | 9 4 | 7 3
Injury Limb injury NOS Skin laceration Thermal burn | 3 2 1 | 2 <1 <1
*Percentage based on female patients only.
** Acute versus other hypersensitivity reactions are defined as occurring within 2 hours post-infusion versus more than 2 hours.

In Study MS2, peripheral edema was more common in patients who received TYSABRI (5% versus 1% in placebo).

Crohn's Disease Clinical Studies

The following serious adverse reactions in the induction Studies CD1 and CD2 [see Clinical Studies (14.2)] were reported more commonly with TYSABRI than placebo and occurred at an incidence of at least 0.3%: intestinal obstruction or stenosis (2% vs. 1% in placebo), acute hypersensitivity reactions (0.5% vs. 0%), abdominal adhesions (0.3% vs. 0%), and cholelithiasis (0.3% vs. 0%). Similar serious adverse reactions were seen in the maintenance Study CD3. Table 3 enumerates adverse reactions that occurred in Studies CD1 and CD2 (median exposure of 2.8 months). Table 4 enumerates adverse reactions that occurred in Study CD3 (median exposure of 11.0 months).

Table 3: Adverse Reactions in Studies CD1 and CD2 (Induction Studies)
Adverse Reactions* | TYSABRI n=983 % | Placebo n=431 %
General Headache Fatigue Arthralgia Influenza-like illness Acute hypersensitivity reactions Tremor | 32 10 8 5 2 1 | 23 8 6 4 <1 <1
Infection Upper respiratory tract infection Vaginal infections** Viral infection Urinary tract infection | 22 4 3 3 | 16 2 2 1
Respiratory Pharyngolaryngeal pain Cough | 6 3 | 4 <1
Gastrointestinal Nausea Dyspepsia Constipation Flatulence Aphthous stomatitis | 17 5 4 3 2 | 15 3 2 2 <1
Skin Rash Dry skin | 6 1 | 4 0
Menstrual Disorder Dysmenorrhea** | 2 | <1
* Occurred at an incidence of at least 1% higher in TYSABRI-treated patients than placebo-treated patients.
** Percentage based on female patients only.

Table 4: Adverse Reactions in Study CD3 (Maintenance Study)
Adverse Reactions* | TYSABRI n=214 % | Placebo n=214 %
General Headache Influenza-like illness Peripheral edema Toothache | 37 11 6 4 | 31 6 3 <1
Infection Influenza Sinusitis Vaginal infections** Viral infection | 12 8 8 7 | 5 4 <1 3
Respiratory Cough | 7 | 5
Gastrointestinal Lower abdominal pain | 4 | 2
Musculoskeletal and Connective Tissue Back pain | 12 | 8
Menstrual Disorder Dysmenorrhea** | 6 | 3
* Occurred at an incidence of at least 2% higher in TYSABRI-treated patients than placebo-treated patients.
** Percentage based on female patients only.

Infections

Progressive Multifocal Leukoencephalopathy (PML) occurred in three patients who received TYSABRI in clinical trials [see Warnings and Precautions (5.1)]. Two cases of PML were observed in the 1869 patients with multiple sclerosis who were treated for a median of 120 weeks. These two patients had received TYSABRI in addition to interferon beta-1a [see Warnings and Precautions (5.1)]. The third case occurred after eight doses in one of the 1043 patients with Crohn's disease who were evaluated for PML. In the postmarketing setting, additional cases of PML have been reported in TYSABRI-treated multiple sclerosis and Crohn's disease patients who were not receiving concomitant immunomodulatory therapy.

In Studies MS1 and MS2 [see Clinical Studies (14.1)], the rate of any type of infection was approximately 1.5 per patient-year in both TYSABRI-treated patients and placebo-treated patients. The infections were predominately upper respiratory tract infections, influenza, and urinary tract infections. In Study MS1, the incidence of serious infection was approximately 3% in TYSABRI-treated patients and placebo-treated patients. Most patients did not interrupt treatment with TYSABRI during infections. The only opportunistic infection in the multiple sclerosis clinical trials was a case of cryptosporidial gastroenteritis with a prolonged course.

In Studies CD1 and CD2 [see Clinical Studies (14.2)], the rate of any type of infection was 1.7 per patient-year in TYSABRI-treated patients and 1.4 per patient-year in placebo-treated patients. In Study CD3, the incidence of any type of infection was 1.7 per patient-year in TYSABRI-treated patients and was similar in placebo-treated patients. The most common infections were nasopharyngitis, upper respiratory tract infection, and influenza. The majority of patients did not interrupt TYSABRI therapy during infections, and recovery occurred with appropriate treatment. Concurrent use of TYSABRI in CD clinical trials with chronic steroids and/or methotrexate, 6-MP, and azathioprine did not result in an increase in overall infections compared to TYSABRI alone; however, the concomitant use of such agents could lead to an increased risk of serious infections.

In Studies CD1 and CD2, the incidence of serious infection was approximately 2.1% in both TYSABRI-treated patients and placebo-treated patients. In Study CD3, the incidence of serious infection was approximately 3.3% in TYSABRI-treated patients and approximately 2.8% in placebo-treated patients.

In clinical studies for CD, opportunistic infections (pneumocystis carinii pneumonia, pulmonary mycobacterium avium intracellulare, bronchopulmonary aspergillosis, and burkholderia cepacia) have been observed in <1% of TYSABRI-treated patients; some of these patients were receiving concurrent immunosuppressants [see Warnings and Precautions (5.6)]. Two serious non-bacterial meningitides occurred in TYSABRI-treated patients compared to none in placebo-treated patients.

Infusion-related Reactions

An infusion-related reaction was defined in clinical trials as any adverse event occurring within two hours of the start of an infusion. In MS clinical trials, approximately 24% of TYSABRI-treated multiple sclerosis patients experienced an infusion-related reaction, compared to 18% of placebo-treated patients. In the controlled CD clinical trials, infusion-related reactions occurred in approximately 11% of patients treated with TYSABRI compared to 7% of placebo-treated patients. Reactions more common in the TYSABRI-treated MS patients compared to the placebo-treated MS patients included headache, dizziness, fatigue, urticaria, pruritus, and rigors. Acute urticaria was observed in approximately 2% of patients. Other hypersensitivity reactions were observed in 1% of patients receiving TYSABRI. Serious systemic hypersensitivity infusion reactions occurred in <1% of patients [see Warnings and Precautions (5.5)]. All patients recovered with treatment and/or discontinuation of the infusion.

Infusion-related reactions that were more common in CD patients receiving TYSABRI than those receiving placebo included headache, nausea, urticaria, pruritus, and flushing. Serious infusion reactions occurred in Studies CD1, CD2, and CD3 at an incidence of <1% in TYSABRI-treated patients.

MS and CD patients who became persistently positive for antibodies to TYSABRI were more likely to have an infusion-related reaction than those who were antibody-negative.

6.2 Immunogenicity

As with all therapeutic proteins, there is a potential for immunogenicity. The detection of antibody formation is highly dependent on the sensitivity and specificity of the assay. Additionally, the observed incidence of antibody (including neutralizing antibody) positivity in an assay may be influenced by several factors including assay methodology, sample handling, timing of sample collection, concomitant medications, and underlying disease. For these reasons, comparison of the incidence of antibodies to natalizumab in the studies described below with the incidence of antibodies in other studies or to other products may be misleading.

Patients in Study MS1 [see Clinical Studies (14.1)] were tested for antibodies to natalizumab every 12 weeks. The assays used were unable to detect low to moderate levels of antibodies to natalizumab. Approximately 9% of patients receiving TYSABRI developed detectable antibodies at least once during treatment. Approximately 6% of patients had positive antibodies on more than one occasion. Approximately 82% of patients who became persistently antibody-positive developed detectable antibodies by 12 weeks. Anti-natalizumab antibodies were neutralizing in vitro.

The presence of anti-natalizumab antibodies was correlated with a reduction in serum natalizumab levels. In Study MS1, the Week 12 pre-infusion mean natalizumab serum concentration in antibody-negative patients was 15 mcg/mL compared to 1.3 mcg/mL in antibody-positive patients. Persistent antibody-positivity resulted in a substantial decrease in the effectiveness of TYSABRI. The risk of increased disability and the annualized relapse rate were similar in persistently antibody-positive TYSABRI-treated patients and patients who received placebo. A similar phenomenon was also observed in Study MS2.

Infusion-related reactions that were most often associated with persistent antibody-positivity included urticaria, rigors, nausea, vomiting, headache, flushing, dizziness, pruritus, tremor, feeling cold, and pyrexia. Additional adverse reactions more common in persistently antibody-positive patients included myalgia, hypertension, dyspnea, anxiety, and tachycardia.

Patients in CD studies [see Clinical Studies (14.2)] were first tested for antibodies at Week 12, and in a substantial proportion of patients, this was the only test performed given the 12-week duration of placebo-controlled studies. Approximately 10% of patients were found to have anti-natalizumab antibodies on at least one occasion. Five percent (5%) of patients had positive antibodies on more than one occasion. Persistent antibodies resulted in reduced efficacy and an increase in infusion-related reactions with symptoms that include urticaria, pruritus, nausea, flushing, and dyspnea.

The long-term immunogenicity of TYSABRI and the effects of low to moderate levels of antibody to natalizumab are unknown [see Warnings and Precautions (5.5), Adverse Reactions (6.1)].

6.3 Postmarketing Experience

The following adverse reactions have been identified during post approval use of TYSABRI. Because these reactions are reported voluntarily from a population of uncertain size, it is not always possible to reliably estimate their frequency or establish a causal relationship to drug exposure.

Blood disorders: hemolytic anemia, thrombocytopenia (including immune thrombocytopenic purpura).

7 DRUG INTERACTIONS

Because of the potential for increased risk of PML and other infections, Crohn's disease patients receiving TYSABRI should not be treated with concomitant immunosuppressants (e.g., 6-mercaptopurine, azathioprine, cyclosporine, or methotrexate) or inhibitors of TNF-α, and corticosteroids should be tapered in those patients with Crohn's disease who are on chronic corticosteroids when they start TYSABRI therapy [see Indications and Usage (1.2), Warnings and Precautions (5.1, 5.6)]. Ordinarily, MS patients receiving chronic immunosuppressant or immunomodulatory therapy should not be treated with TYSABRI [see Indications and Usage (1.1), Warnings and Precautions (5.1, 5.6)].

8 USE IN SPECIFIC POPULATIONS

8.1 Pregnancy

Risk Summary

There are no adequate data on the risk of major birth defects, miscarriage, or other adverse maternal outcomes associated with the use of TYSABRI in pregnant women. Adverse fetal outcomes of neonatal thrombocytopenia and anemia have been reported (see Clinical Considerations). In animal studies, administration of natalizumab during pregnancy produced fetal immunologic and hematologic effects in monkeys at doses similar to the human dose and reduced offspring survival in guinea pigs at doses greater than the human dose. These doses were not maternally toxic but produced the expected pharmacological effects in maternal animals [see Data].

In the U.S. general population, the estimated background risk of major birth defects and miscarriage in clinically recognized pregnancies is 2-4% and 15-20%, respectively. The background risk of major birth defects and miscarriage for the indicated population is unknown.

Clinical Considerations

Fetal/Neonatal Adverse Reactions

Cases of neonatal thrombocytopenia and anemia in infants born to women exposed to TYSABRI during pregnancy were reported in the post-marketing setting [see Warnings and Precautions (5.8)]. Therefore, a CBC should be obtained in neonates who were exposed to TYSABRI in utero.

Data

Animal Data

In developmental toxicity studies conducted in guinea pigs and monkeys, at natalizumab doses up to 30 mg/kg (7 times the recommended human dose based on body weight [mg/kg]), transplacental transfer and in utero exposure of the embryo/fetus was demonstrated in both species.

In a study in which pregnant guinea pigs were administered natalizumab (0, 3, 10, or 30 mg/kg) by intravenous (IV) infusion on alternate days throughout organogenesis (gestation days [GD] 4-30), no effects on embryofetal development were observed.

When pregnant monkeys were administered natalizumab (0, 3, 10, or 30 mg/kg) by IV infusion on alternative days throughout organogenesis (GDs 20-70), serum levels in fetuses at delivery were approximately 35% of maternal serum natalizumab levels. There were no effects on embryofetal development; however, natalizumab-related immunological and hematologic changes were observed in the fetuses at the two highest doses. These changes included decreases in lymphocytes (CD3+ and CD20+), changes in lymphocyte subpopulation percentages, mild anemia, reduced platelet count, increased spleen weights, and reduced liver and thymus weights associated with increased splenic extramedullary hematopoiesis, thymic atrophy, and decreased hepatic hematopoiesis.

In a study in which monkeys were exposed to natalizumab during pregnancy (IV infusion of 30 mg/kg) on alternate days from GD20 to GD70 or GD20 to term, abortions were increased approximately 2-fold compared to controls. In offspring born to mothers administered natalizumab on alternate days from GD20 until delivery, hematologic effects (decreased lymphocyte and platelet counts) were also observed. These effects were reversed upon clearance of natalizumab. There was no evidence of anemia in these offspring. Offspring exposed in utero and during lactation had a normal immune response to challenge with a T-cell dependent antigen.

In a study in which pregnant guinea pigs were exposed to natalizumab (30 mg/kg IV) on alternate dates during GDs 30-64, a reduction in pup survival was observed.

8.2 Lactation

Risk Summary

Natalizumab has been detected in human milk. There are no data on the effects of this exposure on the breastfed infant or the effects of the drug on milk production.

The developmental and health benefits of breastfeeding should be considered along with the mother's clinical need for TYSABRI and any potential adverse effects on the breastfed infant from TYSABRI or from the underlying maternal condition.

8.4 Pediatric Use

Safety and effectiveness in pediatric patients with multiple sclerosis or Crohn's disease below the age of 18 years have not been established. TYSABRI is not indicated for use in pediatric patients.

8.5 Geriatric Use

Clinical studies of TYSABRI did not include sufficient numbers of patients aged 65 years and over to determine whether they respond differently than younger patients. Other reported clinical experience has not identified differences in responses between the elderly and younger patients.

10 OVERDOSAGE

Safety of doses higher than 300 mg has not been adequately evaluated. The maximum amount of TYSABRI that can be safely administered has not been determined.

11 DESCRIPTION

Natalizumab is a recombinant humanized IgG4κ monoclonal antibody produced in murine myeloma cells. Natalizumab contains human framework regions and the complementarity-determining regions of a murine antibody that binds to α4-integrin. The molecular weight of natalizumab is 149 kilodaltons.

TYSABRI (natalizumab) injection is supplied as a sterile, colorless, and clear to slightly opalescent solution for intravenous infusion. Each 15 mL of solution contains 300 mg natalizumab; sodium chloride, USP (123 mg); sodium phosphate, monobasic, monohydrate, USP (17 mg); sodium phosphate, dibasic, heptahydrate, USP (7.24 mg); polysorbate 80, USP/NF (3 mg), in Water for Injection, USP at pH 6.1.

12 CLINICAL PHARMACOLOGY

12.1 Mechanism of Action

Natalizumab binds to the α4-subunit of α4β1 and α4β7 integrins expressed on the surface of all leukocytes except neutrophils, and inhibits the α4-mediated adhesion of leukocytes to their counter-receptor(s). The receptors for the α4 family of integrins include vascular cell adhesion molecule-1 (VCAM-1), which is expressed on activated vascular endothelium, and mucosal addressin cell adhesion molecule-1 (MAdCAM-1) present on vascular endothelial cells of the gastrointestinal tract. Disruption of these molecular interactions prevents transmigration of leukocytes across the endothelium into inflamed parenchymal tissue. In vitro, anti-α4-integrin antibodies also block α4-mediated cell binding to ligands such as osteopontin and an alternatively spliced domain of fibronectin, connecting segment-1 (CS-1). In vivo, natalizumab may further act to inhibit the interaction of α4-expressing leukocytes with their ligand(s) in the extracellular matrix and on parenchymal cells, thereby inhibiting further recruitment and inflammatory activity of activated immune cells.

The specific mechanism(s) by which TYSABRI exerts its effects in multiple sclerosis and Crohn's disease have not been fully defined.

In multiple sclerosis, lesions are believed to occur when activated inflammatory cells, including T-lymphocytes, cross the blood-brain barrier (BBB). Leukocyte migration across the BBB involves interaction between adhesion molecules on inflammatory cells and their counter-receptors present on endothelial cells of the vessel wall. The clinical effect of natalizumab in multiple sclerosis may be secondary to blockade of the molecular interaction of α4β1-integrin expressed by inflammatory cells with VCAM-1 on vascular endothelial cells, and with CS-1 and/or osteopontin expressed by parenchymal cells in the brain. Data from an experimental autoimmune encephalitis animal model of multiple sclerosis demonstrate reduction of leukocyte migration into brain parenchyma and reduction of plaque formation detected by magnetic resonance imaging (MRI) following repeated administration of natalizumab. The clinical significance of these animal data is unknown.

In Crohn's disease, the interaction of the α4β7 integrin with the endothelial receptor MAdCAM-1 has been implicated as an important contributor to the chronic inflammation that is a hallmark of the disease. MAdCAM-1 is mainly expressed on gut endothelial cells and plays a critical role in the homing of T lymphocytes to gut lymph tissue found in Peyer's patches. MAdCAM-1 expression has been found to be increased at active sites of inflammation in patients with CD, which suggests it may play a role in the recruitment of leukocytes to the mucosa and contribute to the inflammatory response characteristic of CD. The clinical effect of natalizumab in CD may therefore be secondary to blockade of the molecular interaction of the α4ß7-integrin receptor with MAdCAM-1 expressed on the venular endothelium at inflammatory foci. VCAM-1 expression has been found to be upregulated on colonic endothelial cells in a mouse model of IBD and appears to play a role in leukocyte recruitment to sites of inflammation. The role of VCAM-1 in CD, however, is not clear.

12.2 Pharmacodynamics

TYSABRI administration increases the number of circulating leukocytes (including lymphocytes, monocytes, basophils, and eosinophils) due to inhibition of transmigration out of the vascular space. TYSABRI does not affect the absolute count of circulating neutrophils [see Warnings and Precautions (5.7)].

12.3 Pharmacokinetics

Multiple Sclerosis (MS) Patients:

In patients with MS, following the repeat intravenous administration of a 300 mg dose of TYSABRI, the mean ± SD maximum observed serum concentration was 110 ± 52 mcg/mL. Mean average steady-state trough concentrations ranged from 23 mcg/mL to 29 mcg/mL. The observed time to steady-state was approximately 24 weeks after every four weeks of dosing. The mean ± SD half-life, volume of distribution, and clearance of natalizumab were 11 ± 4 days, 5.7 ± 1.9 L, and 16 ± 5 mL/hour, respectively.

The effects of covariates such as body weight, age, gender, and presence of anti-natalizumab antibodies on natalizumab pharmacokinetics were investigated in a population pharmacokinetic study (n=2195). Natalizumab clearance increased with body weight in a less than proportional manner such that a 43% increase in body weight resulted in a 32% increase in clearance. The presence of persistent anti-natalizumab antibodies increased natalizumab clearance approximately 3-fold [see Adverse Reactions (6.2)].

Crohn's Disease (CD) Patients:

In patients with CD, following the repeat intravenous administration of a 300 mg dose of TYSABRI, the mean ± SD maximum observed serum concentration was 101 ± 34 mcg/mL. The mean ± SD average steady-state trough concentration was 10 ± 9 mcg/mL. The estimated time to steady-state was approximately 16 to 24 weeks after every four weeks of dosing. The mean ± SD half-life, volume of distribution, and clearance of natalizumab were 10 ± 7 days, 5.2 ± 2.8 L, and 22 ± 22 mL/hour, respectively.

The effects of total body weight, age, gender, race, selected hematology and serum chemistry measures, co-administered medications (infliximab, immunosuppressants, or steroids), and the presence of anti-natalizumab antibodies were investigated in a population pharmacokinetic analysis (n=1156). The presence of anti-natalizumab antibodies was observed to increase natalizumab clearance [see Adverse Reactions (6.2)].

Pharmacokinetics of natalizumab in patients with renal or hepatic insufficiency have not been studied.

13 NONCLINICAL TOXICOLOGY

13.1 Carcinogenesis, Mutagenesis, Impairment of Fertility

No clastogenic or mutagenic effects of natalizumab were observed in the Ames test or in vitro chromosomal aberration assay in human lymphocytes. Natalizumab showed no effects in in vitro assays of α4-integrin positive human tumor line proliferation/cytotoxicity. Xenograft transplantation models in SCID and nude mice with two α4-integrin positive human tumor lines (leukemia, melanoma) demonstrated no increase in tumor growth rates or metastasis resulting from natalizumab treatment.

In male guinea pigs administered natalizumab (0, 3, 10, or 30 mg/kg) by intravenous (IV) infusion on alternate days from 28 days prior to and continuing throughout mating (to untreated females), no effects on fertility were observed. The highest dose tested is 6 times the recommended human dose (RHD) (300 mg) on a body weight (mg/kg) basis.

In a separate study in female guinea pigs (mated with untreated males), natalizumab (0, 3, 10, or 30 mg/kg), administered by IV infusion on alternate days from gestation day (GD) 30 of the first pregnancy through GD 30 of the second pregnancy, resulted in a decrease in pregnancy rate and number of implantations at 30 mg/kg. (Fertility parameters were assessed for the second pregnancy.) The no-effect dose for effects on female fertility (10 mg/kg) is 2 times the RHD on a body weight basis.

14 CLINICAL STUDIES

14.1 Multiple Sclerosis

TYSABRI was evaluated in two randomized, double-blind, placebo-controlled trials in patients with multiple sclerosis. Both studies enrolled patients who experienced at least one clinical relapse during the prior year and had a Kurtzke Expanded Disability Status Scale (EDSS) score between 0 and 5.0. Results for each study are shown in Table 5 and Table 6. Median time on study drug was 120 weeks in each study. In both studies, neurological evaluations were performed every 12 weeks and at times of suspected relapse. Magnetic resonance imaging evaluations for T1-weighted gadolinium (Gd)-enhancing lesions and T2-hyperintense lesions were performed annually.

Study MS1 enrolled patients who had not received any interferon-beta or glatiramer acetate for at least the previous 6 months; approximately 94% had never been treated with these agents. Median age was 37, with a median disease duration of 5 years. Patients were randomized in a 2:1 ratio to receive TYSABRI 300 mg intravenous infusion (n=627) or placebo (n=315) every 4 weeks for up to 28 months (30 infusions).

Study MS2 enrolled patients who had experienced one or more relapses while on treatment with AVONEX® (Interferon beta-1a) 30 mcg intramuscularly (IM) once weekly during the year prior to study entry. Median age was 39, with a median disease duration of 7 years. Patients were evenly randomized to receive TYSABRI 300 mg (n=589) or placebo (n=582) every 4 weeks for up to 28 months (30 infusions). All patients continued to receive AVONEX 30 mcg IM once weekly. The efficacy of TYSABRI alone was not compared with the efficacy of TYSABRI plus AVONEX.

The primary endpoint at 2 years was time to onset of sustained increase in disability, defined as an increase of at least 1 point on the EDSS from baseline EDSS ≥ 1.0 that was sustained for 12 weeks, or at least a 1.5 point increase on the EDSS from baseline EDSS=0 that was sustained for 12 weeks. Time to onset of sustained increase in disability was longer in TYSABRI-treated patients than in placebo-treated patients in Studies MS1 (Figure 1) and MS2. The proportion of patients with increased disability and the annualized relapse rate were also lower in TYSABRI-treated patients than in placebo-treated patients in Studies MS1 and MS2 (Table 5 and Table 6).

Table 5: Clinical and MRI Endpoints in Study MS1 (Monotherapy Study) at 2 Years
 | TYSABRI n=627 | Placebo n=315
CLINICAL ENDPOINTS
Percentage with sustained increase in disability | 17% | 29%
Relative Risk Reduction | 42% (95% CI 23%, 57%)
Annualized relapse rate | 0.22 | 0.67
Relative reduction (percentage) | 67%
Percentage of patients remaining relapse-free | 67% | 41%
MRI ENDPOINTS
New or newly enlarging T2-hyperintense lesions
Median | 0.0 | 5.0
Percentage of patients with*:
0 lesions | 57% | 15%
1 lesion | 17% | 10%
2 lesions | 8% | 8%
3 or more lesions | 18% | 68%
Gd-enhancing lesions
Median | 0.0 | 0.0
Percentage of patients with:
0 lesions | 97% | 72%
1 lesion | 2% | 12%
2 or more lesions | 1% | 16%
All analyses were intent-to-treat. For each endpoint, p<0.001. Determination of p-values: Increase in disability by Cox proportional hazards model adjusted for baseline EDSS and age; relapse rate by Poisson regression adjusting for baseline relapse rate, EDSS, presence of Gd-enhancing lesions, age; percentage relapse-free by logistic regression adjusting for baseline relapse rate; and lesion number by ordinal logistic regression adjusting for baseline lesion number.
Annualized relapse rate is calculated as the number of relapses for each subject divided by the number of years followed in the study for that subject. The value reported is the mean across all subjects.
*Values do not total 100% due to rounding.

Table 6: Clinical and MRI Endpoints in Study MS2 (Add-On Study) at 2 Years
 | TYSABRI plus AVONEX n= 589 | Placebo plus AVONEX n=582
CLINICAL ENDPOINTS
Percentage with sustained increase in disability | 23% | 29%
Relative Risk Reduction | 24% (95% CI 4%, 39%)
Annualized relapse rate | 0.33 | 0.75
Relative reduction (percentage) | 56%
Percentage of patients remaining relapse-free | 54% | 32%
MRI ENDPOINTS
New or newly enlarging T2-hyperintense lesions
Median | 0.0 | 3.0
Percentage of patients with*:
0 lesions | 67% | 30%
1 lesion | 13% | 9%
2 lesions | 7% | 10%
3 or more lesions | 14% | 50%
Gd-enhancing lesions
Median | 0.0 | 0.0
Percentage of patients with*:
0 lesions | 96% | 75%
1 lesion | 2% | 12%
2 or more lesions | 1% | 14%
All analyses were intent-to-treat. For disability accumulation p=0.024, for all other endpoints, p<0.001. Determination of p-values: Increase in disability by Cox proportional hazards model adjusted for baseline EDSS; relapse rate by Poisson regression adjusting for baseline relapse rate, EDSS, presence of Gd-enhancing lesions, age; percentage relapse-free by logistic regression adjusting for baseline relapse rate; and lesion number by ordinal logistic regression adjusting for baseline lesion number.
Annualized relapse rate is calculated as the number of relapses for each subject divided by the number of years followed in the study for that subject. The value reported is the mean across all subjects.
*Values do not total 100% due to rounding.

Figure 1: Time to Increase in Disability Sustained for 12 Weeks in Study MS1

14.2 Crohn's Disease

The safety and efficacy of TYSABRI were evaluated in three randomized, double-blind, placebo-controlled clinical trials in 1414 adult patients with moderately to severely active Crohn's disease (Crohn's Disease Activity Index [CDAI] ≥220 and ≤450) [see References (15)]. Concomitant inhibitors of TNF-α were not permitted. Concomitant stable doses of aminosalicylates, corticosteroids, and/or immunosuppressants (e.g., 6-mercatopurine, azathioprine, or methotrexate) were permitted, and 89% of patients continued to receive at least one of these medications. Although permitted in the clinical trials, combination therapy with immunosuppressants is not recommended [see Indications and Usage (1.2)]. Overall, approximately two-thirds of patients were not taking concomitant immunosuppressants, and approximately one-third of patients were taking neither concomitant immunosuppressants nor concomitant corticosteroids.

Induction of clinical response (defined as ≥70-point decrease in CDAI from baseline) was evaluated in two studies. In Study CD1, 896 patients were randomized 4:1 to receive three monthly infusions of either 300 mg TYSABRI or placebo. Clinical results were assessed at Week 10, and patients with incomplete information were considered as not having a clinical response. At Week 10, 56% of the 717 patients receiving TYSABRI were in response compared to 49% of the 179 patients receiving placebo (treatment effect: 7%; 95% confidence interval (CI): [-1%, 16%]; p=0.067). In a post hoc analysis of the subset of 653 patients with elevated baseline C-reactive protein (CRP), indicative of active inflammation, 57% of TYSABRI patients were in response compared to 45% of those receiving placebo (treatment effect: 12%; 95% CI: [3%, 22%]; nominal p=0.01).

In the second induction trial, Study CD2, only patients with elevated serum C-reactive Protein (CRP) were studied. A total of 509 patients were randomized 1:1 to receive three monthly infusions of either 300 mg TYSABRI or placebo. In Study CD2, in contrast to Study CD1, clinical response and clinical remission (defined as CDAI score <150) were required to be met at both Weeks 8 and 12, rather than at a single time-point; patients with incomplete information were considered as not having a response (Table 7).

Table 7: Induction of Clinical Response and Remission in Study CD2
 | TYSABRI n=259 | Placebo n=250 | Treatment Difference (95% CI)
Clinical Response at: Week 8 Week 12 Both Weeks 8 & 12* | 56% 60% 48% | 40% 44% 32% | 16% (8%, 26%) 16% (7%, 25%) 16% (7%, 24%)
Clinical Remission at: Week 8 Week 12 Both Weeks 8 & 12* | 32% 37% 26% | 21% 25% 16% | 11% (3%, 19%) 12% (4%, 21%) 10% (3%, 18%)
*p <0.005
Response is defined as a ≥70-point reduction in CDAI score from baseline.
Remission is defined as CDAI <150.

In studies CD1 and CD2, for subgroups defined by prior use of, or by inadequate response to prior therapies (i.e., corticosteroids, immunosuppressants, and inhibitors of TNF-α), the treatment effect was generally similar to that seen in the whole study population. In the subgroup of patients that were taking neither concomitant immunosuppressants nor concomitant corticosteroids, the treatment effect was generally similar to that seen in the whole study population. Patients with inadequate response to inhibitors of TNF-α appeared to have lower clinical response and lower clinical remission in both the treatment and placebo groups. For patients in Study CD2 with an inadequate response to prior treatment with inhibitors of TNF-α, clinical response at both Weeks 8 and 12 was seen in 38% of those randomized to TYSABRI, and clinical remission at both Weeks 8 and 12 was seen in 17%.

Maintenance therapy was evaluated in Study CD3. In this study, 331 patients from Study CD1 that had had a clinical response to TYSABRI at both Weeks 10 and 12 were re-randomized 1:1 to treatment with continuing monthly infusions of either 300 mg TYSABRI or placebo.

Maintenance of response was assessed by the proportion of patients who did not lose clinical response at any study visit for an additional 6 and 12 months of treatment (i.e., Month 9 and Month 15 after initial treatment with TYSABRI). The study also assessed the proportion of patients who did not lose clinical remission at any study visit within the subset of those who were in remission at study entry. Requiring maintenance of response or remission at each visit, as opposed to just at Month 9 or Month 15, may result in lower proportions meeting endpoint criteria, and may make a comparison of these results with those of other products used to treat Crohn's disease misleading (Table 8).

Table 8: Maintenance of Clinical Response and Remission in Study CD3
 | TYSABRI | Placebo | Treatment Difference (95% CI)
Clinical Response through: Month 9* Month 15 | n=164 61% 54% | n=167 29% 20% | 32% (21%, 43%) 34% (23%, 44%)
Clinical Remission through: Month 9* Month 15 | n=128† 45% 40% | n=118† 26% 15% | 19% (6%, 31%) 25% (13%, 36%)
*p<0.005
†Number of patients included for analysis of “through” Month 9 and Month 15 includes only those in remission upon entry into Study CD3.
Response is defined as CDAI <220 and a ≥70-point reduction in CDAI score compared to Baseline from Study CD1.
Remission is defined as CDAI <150.

For subgroups in study CD3 defined by prior use of, or by inadequate response to prior therapies (i.e., corticosteroids, immunosuppressants, and inhibitors of TNF-α), the treatment effect was generally similar to that seen in the whole study population. In the subgroup of patients that were taking neither concomitant immunosuppressants nor concomitant corticosteroids, the treatment effect was generally similar to that seen in the whole study population. Patients with inadequate response to inhibitors of TNF-α appeared to have lower maintenance of clinical response and lower maintenance of clinical remission in both the treatment and placebo groups. For patients in study CD3 with an inadequate response to prior treatment with inhibitors of TNF-α, maintenance of clinical response through Month 9 was seen in 52% of those randomized to TYSABRI, and maintenance of clinical remission through Month 9 was seen in 30%.

Given the requirement to discontinue chronic steroids it is important to note that in the subgroup of patients (n=65) who were receiving corticosteroid medication at baseline, responded to TYSABRI in Study CD1, and were re-randomized to TYSABRI in Study CD3, approximately two-thirds were able to discontinue steroids within 10 weeks of initiating a steroid taper.

15 REFERENCES

- Best WR, Becktel JM, Singleton JW, Kern F: Development of a Crohn's Disease Activity Index, National Cooperative Crohn's Disease Study. Gastroenterology 1976; 70(3): 439-444.

16 HOW SUPPLIED/STORAGE AND HANDLING

TYSABRI (natalizumab) injection, a sterile, preservative-free, colorless and clear to slightly opalescent solution for dilution prior to intravenous infusion, is supplied as one 300 mg/15 mL (20 mg/mL) single-dose vial per carton (NDC 64406-008-01).

TYSABRI is available only through registered infusion centers participating in the TOUCH® Prescribing Program. To locate these infusion centers, contact Biogen at 1-800-456-2255.

TYSABRI single-dose vials must be refrigerated between 2°C to 8°C (36°F to 46°F). Do not use beyond the expiration date stamped on the carton and vial label. DO NOT SHAKE OR FREEZE. Protect from light.

Store diluted TYSABRI solution refrigerated at 2°C to 8°C (36°F to 46°F) [see Dosage and Administration (2.3)]

17 PATIENT COUNSELING INFORMATION

Advise the patient to read the FDA-approved patient labeling (Medication Guide).

General Counseling Information

Counsel patients to understand the risks and benefits of TYSABRI before an initial prescription is written. The patient may be educated by either the enrolled prescriber or a healthcare provider under that prescriber's direction. INSTRUCT PATIENTS USING TYSABRI TO:

- Read the Medication Guide before starting TYSABRI and before each TYSABRI infusion.
- Promptly report any new or continuously worsening symptoms that persist over several days to their prescriber [see Warnings and Precautions (5.1)].
- Inform all of their physicians that they are receiving TYSABRI.
- Plan to see their prescriber three months after the first infusion, six months after the first infusion, every six months thereafter, and for at least six months after discontinuing TYSABRI.

Progressive Multifocal Leukoencephalopathy

Inform patients that Progressive Multifocal Leukoencephalopathy (PML) has occurred in patients who received TYSABRI. Instruct the patient of the importance of contacting their doctor if they develop any symptoms suggestive of PML. Instruct the patient that typical symptoms associated with PML are diverse, progress over days to weeks, and include progressive weakness on one side of the body or clumsiness of limbs, disturbance of vision, and changes in thinking, memory, and orientation leading to confusion and personality changes. Instruct the patient that the progression of deficits usually leads to death or severe disability over weeks or months.

Instruct patients to continue to look for new signs and symptoms suggestive of PML for approximately 6 months following discontinuation of TYSABRI [see Warnings and Precautions (5.1)].

TYSABRI TOUCH® Prescribing Program

Advise the patient that TYSABRI is only available through a restricted program called the TOUCH® Prescribing Program. Inform the patient of the following requirements:

Patients must read the Medication Guide and sign the Patient Enrollment Form. Advise patients that TYSABRI is available only from certified pharmacies and infusion centers participating in the program [see Warnings and Precautions (5.2)].

Herpes Infections

Inform patients that TYSABRI increases the risk of developing encephalitis and meningitis, which could be fatal, and acute retinal necrosis, which could lead to blindness, caused by the family of herpes viruses (e.g., herpes simplex and varicella zoster viruses). Instruct patients to immediately report any possible symptoms of encephalitis and meningitis (such as fever, headache, and confusion) or acute retinal necrosis (such as decreased visual acuity, eye redness, or eye pain) [see Warnings and Precautions (5.3)].

Hepatotoxicity

Inform patients that TYSABRI may cause liver injury. Instruct patients treated with TYSABRI to report promptly any symptoms that may indicate liver injury, including fatigue, anorexia, right upper abdominal discomfort, dark urine, or jaundice [see Warnings and Precautions (5.4)].

Hypersensitivity Reactions

Instruct patients to report immediately if they experience symptoms consistent with a hypersensitivity reaction (e.g., urticaria with or without associated symptoms) during or following an infusion of TYSABRI [see Warnings and Precautions (5.5)].

Immunosuppression/Infections

Inform patients that TYSABRI may lower the ability of their immune system to fight infections. Instruct the patient of the importance of contacting their doctor if they develop any symptoms of infection [see Warnings and Precautions (5.6)].

Hematological Abnormalities

Inform patients that Tysabri may cause a low platelet count, which can cause severe bleeding that may be life-threatening. Instruct patients to report any symptoms that may indicate thrombocytopenia, such as easy bruising, prolonged bleeding from cuts, petechiae, abnormally heavy menstrual periods, or bleeding from the nose or gums that is new. Advise patients that TYSABRI may cause low platelet or red blood cell counts in neonates exposed to TYSABRI during pregnancy [see Warnings and Precuations (5.8)].

Pregnancy

Instruct patients that if they become pregnant or plan to become pregnant while taking TYSABRI they should inform their healthcare provider [see Use in Specific Populations (8.1)].

I61061-31

TYSABRI (natalizumab)
Manufactured by:
Biogen Inc.
Cambridge, MA 02142 USA
US License No. 1697

© 2015-2025 Biogen Inc. All rights reserved.
U.S. Patent Numbers: 5,840,299; 6,602,503

MEDICATION GUIDE
TYSABRI® (tie-SA-bree)
(natalizumab)
injection, for intravenous use

Read this Medication Guide before you start receiving TYSABRI and before you receive each dose. There may be new information. This Medication Guide does not take the place of talking to your doctor about your medical condition or your treatment.

What is the most important information I should know about TYSABRI?

- TYSABRI increases your chance (risk) of getting a rare brain infection that usually leads to death or severe disability. This infection is called progressive multifocal leukoencephalopathy (PML). If PML happens, it usually happens in people with weakened immune systems.
  - There is no known treatment, prevention, or cure for PML.
  - Your chance of getting PML may be higher if you are also being treated with other medicines that can weaken your immune system, including other treatments for Multiple Sclerosis (MS) and Crohn's disease (CD). You should not take certain medicines that weaken your immune system at the same time you are taking TYSABRI. Even if you use TYSABRI alone to treat your MS or CD, you can still get PML.
  - Your risk of getting PML is higher if you:
    - have been infected by the John Cunningham Virus (JCV). JCV is a common virus that is harmless in most people but can cause PML in people who have weakened immune systems, such as people taking TYSABRI. Most people who are infected by JCV do not know it or do not have any symptoms. This infection usually happens in childhood. Before you start receiving TYSABRI or during your treatment, your doctor may do a blood test to check if you have been infected by JCV.
    - have received TYSABRI for a long time, especially longer than 2 years
    - have received certain medicines that can weaken your immune system before you start receiving TYSABRI
    Your risk of getting PML is greatest if you have all 3 risk factors listed above. There may be other risk factors for getting PML during TYSABRI treatment that we do not know about yet. Your doctor should discuss the risks and benefits of TYSABRI treatment with you before you decide to receive TYSABRI. See “What are the possible side effects of TYSABRI?”
  - While you receive TYSABRI, and for 6 months after you stop receiving TYSABRI, it is important that you call your doctor right away if you have any new or worsening medical problems that have lasted several days.
    These may be new or sudden and include problems with:
    - thinking
    - balance
    - eyesight
    - weakness on 1 side of your body
    - strength
    - using your arms and legs

Tell all your doctors that you are receiving TYSABRI.

- Because of your risk of getting PML while you receive TYSABRI, TYSABRI is available only through a restricted distribution program called the TOUCH® Prescribing Program. To receive TYSABRI, you must talk to your doctor and understand the risks and benefits of TYSABRI and agree to follow all of the instructions in the TOUCH® Prescribing Program.
  - TYSABRI is only:
    - prescribed by doctors who are enrolled in the TOUCH® Prescribing Program
    - given by an infusion nurse from an infusion center that is enrolled in the TOUCH® Prescribing Program
    - given to people who are enrolled in the TOUCH® Prescribing Program
  - Before you receive TYSABRI, your doctor will:
    - explain the TOUCH® Prescribing Program to you
    - have you sign the TOUCH® Patient Enrollment Form

What is TYSABRI?
TYSABRI is a prescription medicine used to treat adults with:

- relapsing forms of Multiple Sclerosis (MS), to include clinically isolated syndrome, relapsing-remitting disease and active secondary progressive disease. TYSABRI increases the risk of PML. When starting and continuing treatment with TYSABRI, it is important that you discuss with your doctor whether the expected benefit of TYSABRI is enough to outweigh this risk. See “What is the most important information I should know about TYSABRI?”
- moderate to severe Crohn's disease (CD). TYSABRI is used:
  - to reduce signs and symptoms of CD
  - in people who have not been helped enough by, or cannot use the usual CD medicines and medicines called tumor necrosis factor (TNF) inhibitors.
- It is not known if TYSABRI is safe and effective in children under 18 years of age.

Who should not receive TYSABRI?
Do not receive TYSABRI if you:

- have PML
- are allergic to natalizumab or any of the ingredients in TYSABRI. See the end of this Medication Guide for a complete list of ingredients in TYSABRI.

Talk to your doctor before receiving TYSABRI if you have any of these conditions.

What should I tell my doctor before receiving each dose of TYSABRI?
Before you receive TYSABRI, tell your doctor if you:

- have medical conditions that can weaken your immune system, including:
  - HIV infection or AIDS
  - leukemia or lymphoma
  - an organ transplant
  - other medical conditions that can weaken your immune system

- have any new or worsening medical problems that have lasted several days. These may be new or sudden and include problems with:
  - thinking
  - strength
  - eyesight
  - weakness on 1 side of your body
  - balance
  - using your arms and legs

- have had hives, itching or trouble breathing during or after receiving a dose of TYSABRI
- have a fever or infection (including shingles or any unusually long lasting infection)
- are pregnant or plan to become pregnant. TYSABRI may cause low platelets (thrombocytopenia) and low red blood cells (anemia) in your newborn baby if you take TYSABRI while you are pregnant. It is not known if TYSABRI can cause birth defects.
- are breastfeeding or plan to breastfeed. TYSABRI can pass into your breast milk. It is not known if the TYSABRI that passes into your breast milk can harm your baby. Talk to your doctor about the best way to feed your baby while you receive TYSABRI.

Tell your doctor about all the medicines you take, including prescription and over-the-counter medicines, vitamins and herbal supplements. Especially tell your doctor if you take medicines that can weaken your immune system. Ask your doctor if you are not sure.
Know the medicines you take. Keep a list of them to show your doctor and pharmacist when you get a new medicine.

How should I receive TYSABRI?

- TYSABRI is given 1 time every 4 weeks through a needle placed in your vein (IV infusion). Each infusion will last about 1 hour.
- Before each TYSABRI dose you will be asked questions to make sure TYSABRI is still right for you.

What are the possible side effects of TYSABRI?

TYSABRI may cause serious side effects, including:

- See “What is the most important information I should know about TYSABRI?”
- Herpes Infections. TYSABRI may increase your risk of getting an infection of the brain or the covering of your brain and spinal cord (encephalitis or meningitis) caused by herpes viruses that may lead to death. Call your doctor right away if you have sudden fever, severe headache, or if you feel confused after receiving TYSABRI. Herpes infections of the eye, causing blindness in some patients, have also occurred. Call your doctor right away if you have changes in vision, eye redness, or eye pain.
- Liver damage. Symptoms of liver damage can include:
  - yellowing of the skin and eyes (jaundice)
  - unusual darkening of the urine
  - nausea
  - feeling tired or weak
  - vomiting

Call your doctor right away if you have symptoms of liver damage. Your doctor can do blood tests to check for liver damage.

- Allergic reactions, including serious allergic reactions. Symptoms of an allergic reaction can include:
  - hives
  - dizziness
  - nausea
  - itching
  - wheezing
  - flushing of skin
  - trouble breathing
  - chills
  - low blood pressure
  - chest pain
  - rash

Serious allergic reactions usually happen within 2 hours of the start of your infusion, but they can happen at any time after you receive TYSABRI.
Tell your doctor right away if you have any symptom of an allergic reaction, even if it happens after your infusion. You may need treatment if you are having an allergic reaction.

- Infections. TYSABRI may increase your chance of getting an unusual or serious infection because TYSABRI can weaken your immune system. You have a higher risk of getting infections if you also take other medicines that can weaken your immune system.
- Low platelet counts. TYSABRI may cause the number of platelets in your blood to be reduced. Call your healthcare provider if you have any of the following symptoms:
  - easy bruising - heavier menstrual periods than are normal - bleeding from your gums or nose that is new or takes longer than usual to stop - bleeding from a cut that is hard to stop | - small scattered red spots on your skin that are red, pink, or purple

The most common side effects of TYSABRI include:

- headache
- lung infection
- vaginitis
- stomach area pain

- feeling tired
- depression
- rash

- urinary tract infection
- pain in your arm and legs
- nose and throat infections

- joint pain
- diarrhea
- nausea

Tell your doctor about any side effect that bothers you or that does not go away.
These are not all the possible side effects of TYSABRI. Ask your doctor for more information.
Call your doctor for medical advice about side effects. You may report side effects to FDA at 1-800-FDA-1088.

General information about the safe and effective use of TYSABRI.
Medicines are sometimes prescribed for purposes other than those listed in a Medication Guide.
This Medication Guide summarizes the most important information about TYSABRI. If you would like more information, talk with your doctor. You can ask your pharmacist or doctor for information about TYSABRI that is written for healthcare professionals.
For more information, go to www.TYSABRI.com or call 1-800-456-2255.

What are the ingredients in TYSABRI?
Active ingredient: natalizumab
Inactive Ingredients: sodium chloride, sodium phosphate, monobasic, monohydrate; sodium phosphate, dibasic, heptahydrate; polysorbate 80, and water for injection
Manufactured by: Biogen Inc.; Cambridge, MA 02142 USA

This Medication Guide has been approved by the U.S. Food and Drug Administration.

Revised 3/2025

PACKAGE LABEL - PRINCIPAL DISPLAY PANEL - Vial Label

NDC 64406-008-01

TYSABRI®

(natalizumab)

300 mg/ 15 mL

(20 mg/mL)

For Intravenous

Infusion Only. Must be diluted prior to use.

Usual Dosage: See prescribing information.

Manufactured by:

Biogen Inc.

Cambridge, MA 02142 USA

U.S. License # 1697

PACKAGE LABEL - PRINCIPAL DISPLAY PANEL - Carton Label

NDC 64406-008-01

TYSABRI®

(natalizumab)

300 mg/ 15 mL (20 mg/mL)

For Intravenous Infusion Only

Must be diluted prior to use

ATTENTION PHARMACIST:

Each patient is required to receive

the enclosed Medication Guide.

Rx Only